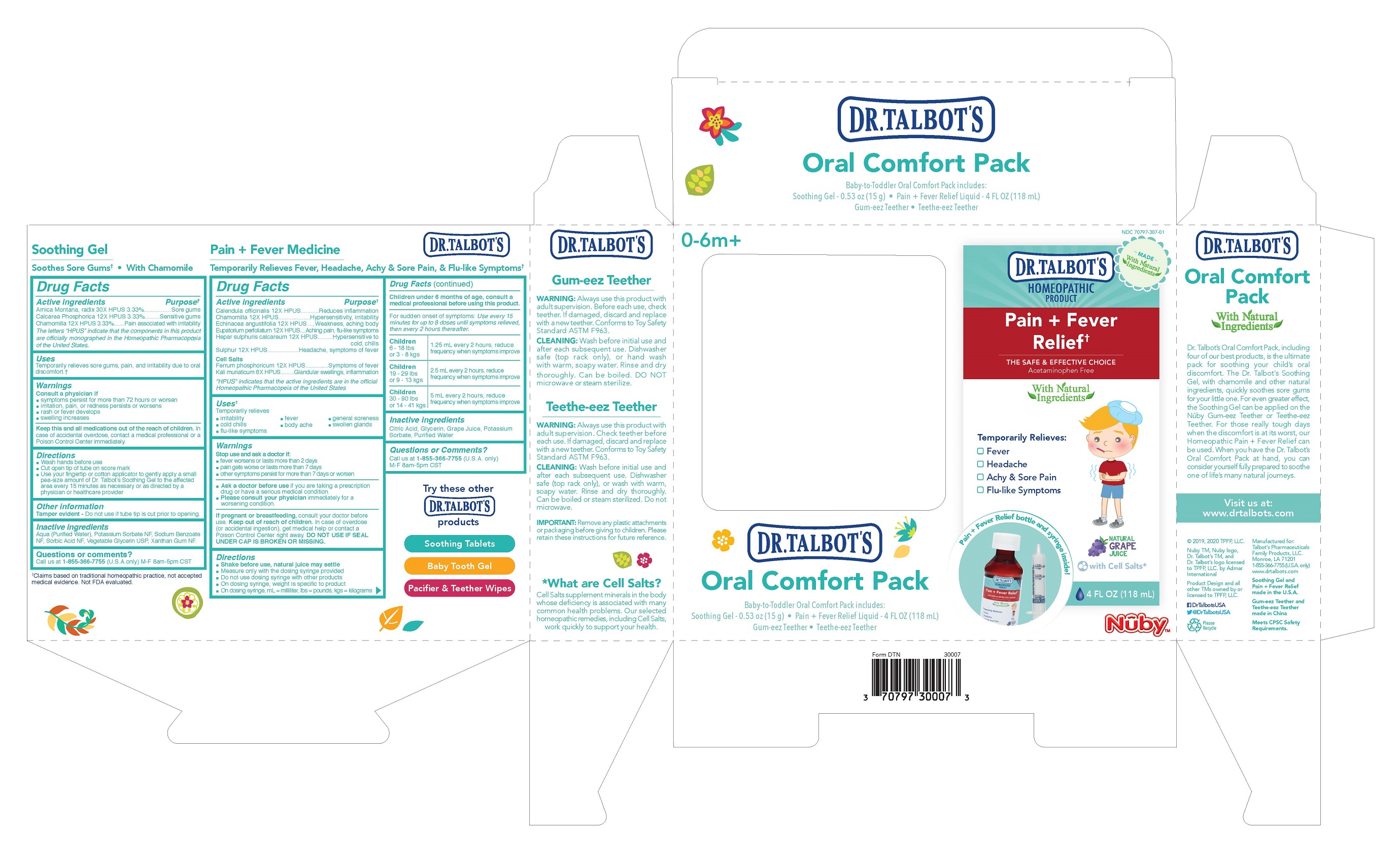 DRUG LABEL: Dr. Talbots Oral Comfort Pack
NDC: 71240-307 | Form: KIT | Route: TOPICAL
Manufacturer: Ningbo Longwell Baby Products Co.,Ltd.
Category: homeopathic | Type: HUMAN OTC DRUG LABEL
Date: 20220222

ACTIVE INGREDIENTS: ARNICA MONTANA ROOT 30 [hp_X]/15 g; TRIBASIC CALCIUM PHOSPHATE 12 [hp_X]/15 g; MATRICARIA RECUTITA 12 [hp_X]/15 g; COSMOS SULPHUREUS FLOWERING TOP 12 [hp_X]/118 mL; CALCIUM SULFIDE 12 [hp_X]/118 mL; CALENDULA OFFICINALIS FLOWERING TOP 12 [hp_X]/118 mL; FERROSOFERRIC PHOSPHATE 12 [hp_X]/118 mL; ECHINACEA ANGUSTIFOLIA 12 [hp_X]/118 mL; POTASSIUM CHLORIDE 6 [hp_X]/118 mL; EUPATORIUM PERFOLIATUM FLOWERING TOP 12 [hp_X]/118 mL; MATRICARIA CHAMOMILLA 12 [hp_X]/118 mL
INACTIVE INGREDIENTS: XANTHAN GUM; WATER; SODIUM BENZOATE; POTASSIUM SORBATE; SORBIC ACID; GLYCERIN; CONCORD GRAPE JUICE; CITRIC ACID MONOHYDRATE; POTASSIUM SORBATE; GLYCERIN; WATER

Active Ingredients

Calendula officinalis 12X HPUS

Chamomilla 12X HPUS

Echinacea angustifolia 12X HPUS

Eupatorium perfoliatum 12X HPUS

Hepar sulphuris calcareum 12X HPUS

Sulphur 12X HPUS

Cell Salts

Ferrum phosphoricum 12X HPUS

Kali muriaticum 6X HPUS

Purpose

Reduces inflammation

Hypersensitivity, irritability

Weakness, aching body

Aching pain, flu-like symptoms

Hypersensitive to cold, chills

Headache, symptoms of fever

Symptoms of fever

Glandular swellings, inflammation

INDICATIONS AND USAGE

Temporarily relieves

- irritability
- cold chills
- flu-like symptoms
- fever
- body ache
- general soreness
- swollen glands

Stop use and ask doctor if:

fever wosens or lasts more than 2 days
pain gets worse or lasts more than 7 days
other symptoms persist for more than 7 days or worsen
Ask a doctor before use if you are taking a prescription drug or have a serious medical condition.
Please consult your physician immediately for a worsening condition.

PREGNANCY OR BREAST FEEDING

If pregnant or breastfeeding, consult your doctor before use.

Keep out of reach of children. In case of overdose (or accidental ingestion), get medical help or contact a Poison Control Center right away.

DOSAGE AND ADMINISTRATION

Shake before use, natural juice may settle
Measure only with the dosing syringe provided
Do not use dosing syringe with other products
On dosing syringe, weight is specific to product
On dosing syringe, ml = milliliter, lbs = pounds, kgs = kilograms

Children under 6 months of age, consult a medical professional before using this product.

For sudden onset of symptoms: Use every 15 minutes for up to 8 doses until symptoms relieved, then every 2 hours thereafter.

Children 6 - 18 lbs or 3 - 8 kgs

1.25 ml every 2 hours, reduce frequency when symptoms improve

Children 19 - 29 lbs or 9 - 13 kgs

2.5 ml every 2 hours, reduce frequency when symptoms improve

Children 30 - 90 lbs or 14 - 41 kgs

5 ml every 2 hours, reduce frequency when symptoms improve

Inactive ingredients

Citric acid, glycerin, grape juice, potassium sorbate, purified water

Questions or Comments?

Call us at 1-855-366-7755 (U.S.A. only) M-F 8am-5pm CST

Active ingredients

Arnica Montana, radix 30X HPUS 3.33%

Calcarea Phosphorica 12X HPUS 3.33%

Chamomilla 12X HPUS 3.33%

The letters “HPUS” indicate that the components in this product are officially monographed in the Homeopathic Pharmacopoeia of the United States.

Purpose†

sore gums

sensitive gums

pain associated with irritability

KEEP OUT OF REACH OF CHILDREN

Keep this and all medications out of the reach of children. In case of accidental overdose contact a medical professional or a Poison Control Center immediately.

Directions

• Wash hands before use.

• Cut open tip of tube on score mark.

• Use your fingertip or cotton applicator to gently apply a small pea-size amount of Dr. Talbot's Soothing Gel to the affected area every 15 minutes as necessary or as directed by a physician or healthcare provider.

Other Information

Tamper evident - Do not use if tube tip is cut prior to opening.

Inactive ingredients

Aqua (Purified Water), Potassium Sorbate NF, Sodium Benzoate NF, Sorbic Acid NF, Vegetable Glycerin USP, Xanthan Gum NF.